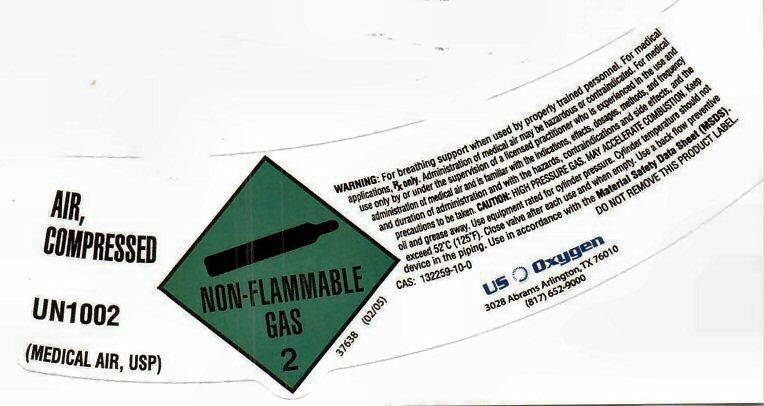 DRUG LABEL: AIR, COMPRESSED
NDC: 54632-003 | Form: GAS
Manufacturer: U.S. Oxygen and Supply, LLC
Category: prescription | Type: HUMAN PRESCRIPTION DRUG LABEL
Date: 20140221

ACTIVE INGREDIENTS: OXYGEN 21 L/100 L
INACTIVE INGREDIENTS: NITROGEN

AIR, COMPRESSED (MEDICAL AIR)

AIR, COMPRESSED UN1002 (MEDICAL AIR, USP) NON-FLAMMABLE GAS 2 37638 (02/05)
WARNING: For breathing support when used by properly trained personnel. For medical applications, Rx only.
Administration of medical air may be hazardous or contraindicated. For medical use only by or under the supervision
of a licensed practitioner who is experienced in the use and administration of medical air and is familiar with
the indications, effects, dosages, methods, and frequency and duration of administration, and with the hazards,
contraindications, and side effects and the precautions to be taken. CAUTION: HIGH PRESSURE GAS. MAY ACCELERATE COMBUSTION. Keep oil and grease away. Use equipment rated for cylinder pressure. Cylinder temperature should not exceed
52° C (125° F). Close valve after each use and when empty. Use a back flow preventive device in
the piping. Use in accordance with the Material Safety Data Sheet (MSDS).
CAS: 132259-10-0 DO NOT REMOVE THIS PRODUCT LABEL

US Oxygen
3028 Abrams Arlington TX 76010 (817) 652-9000